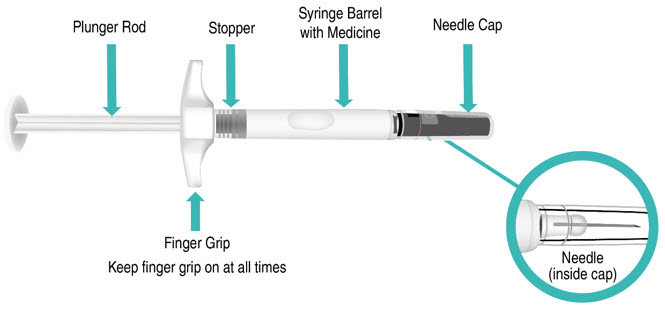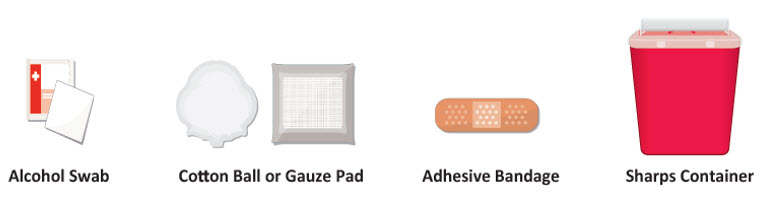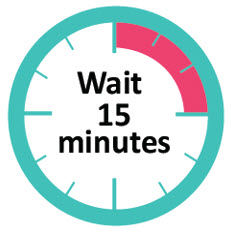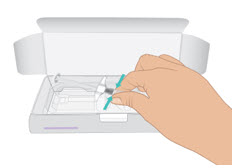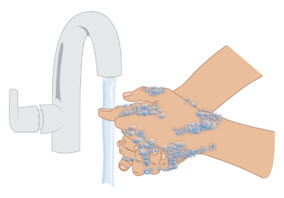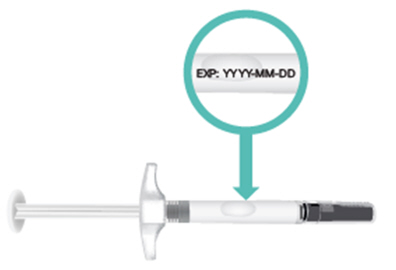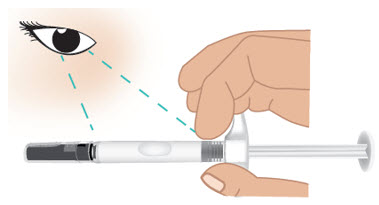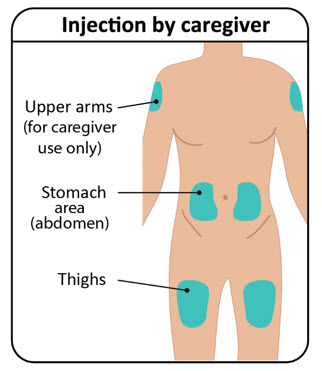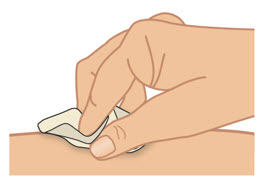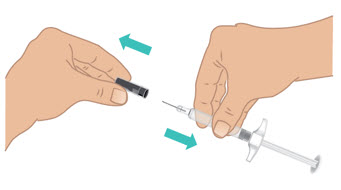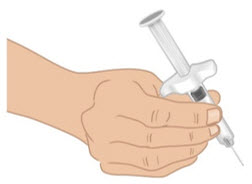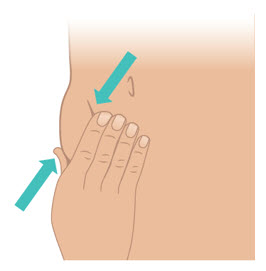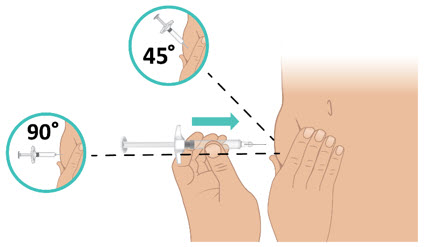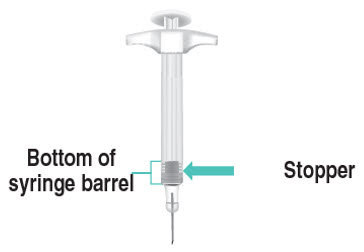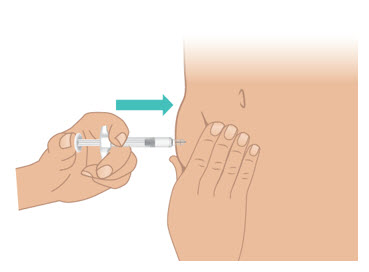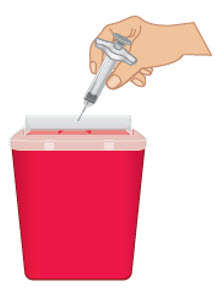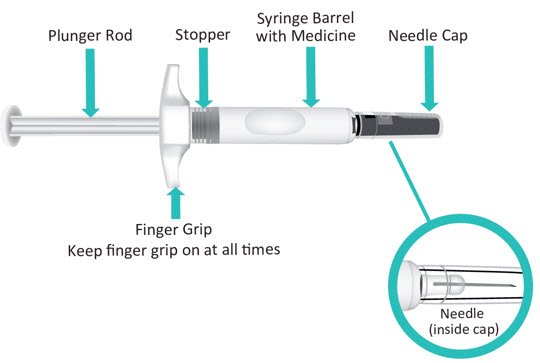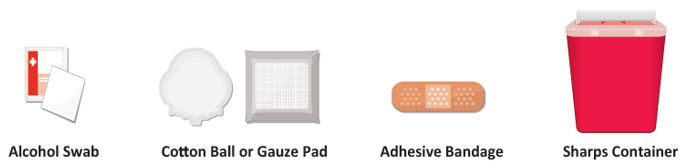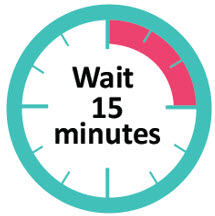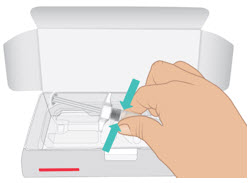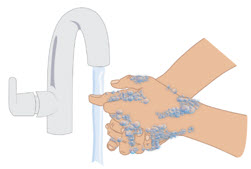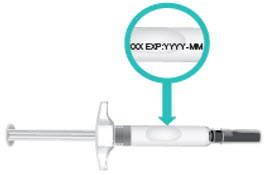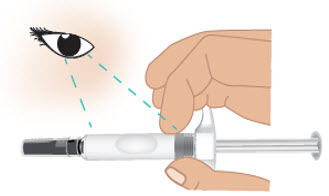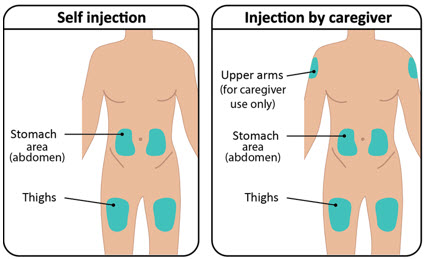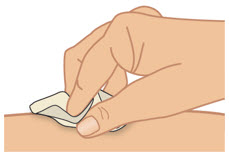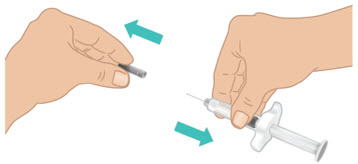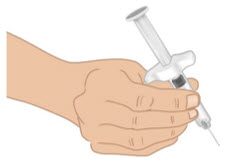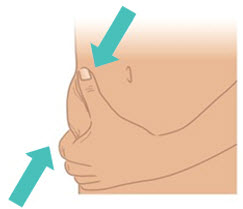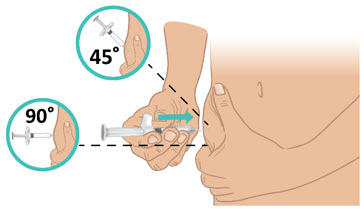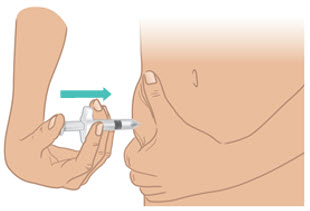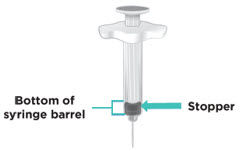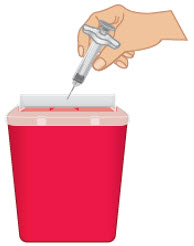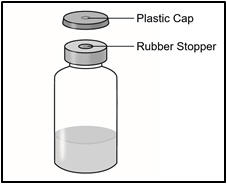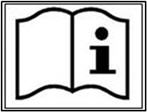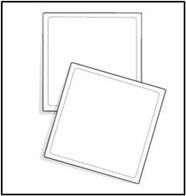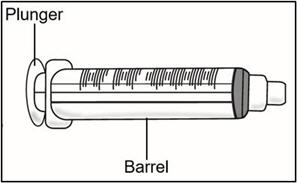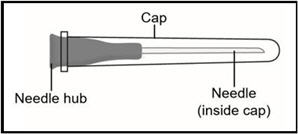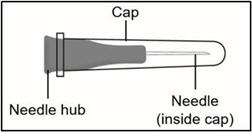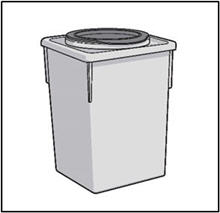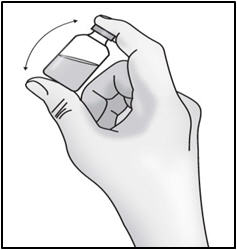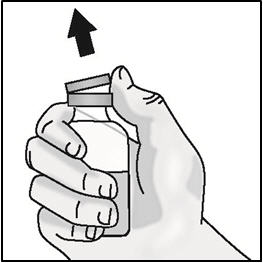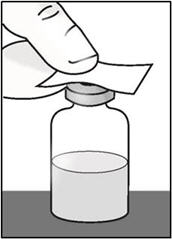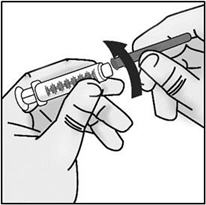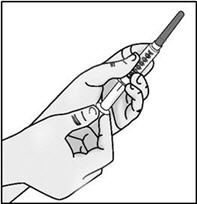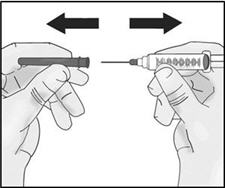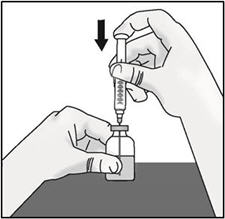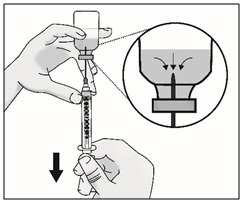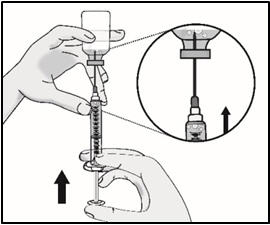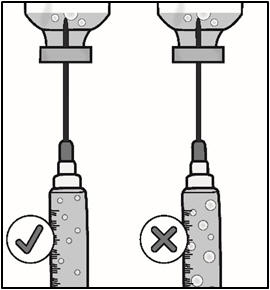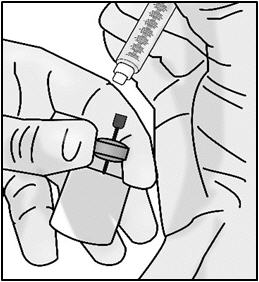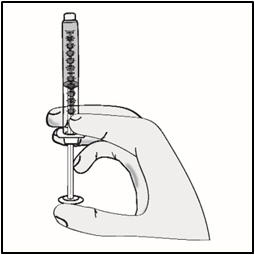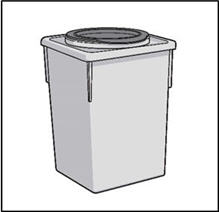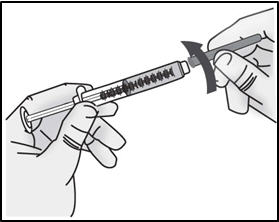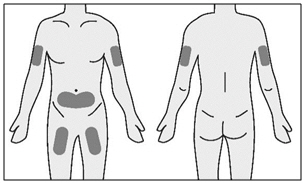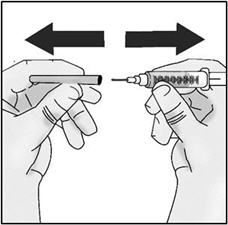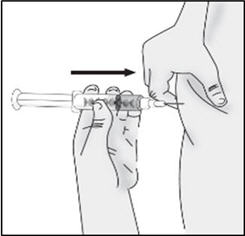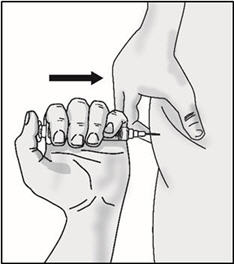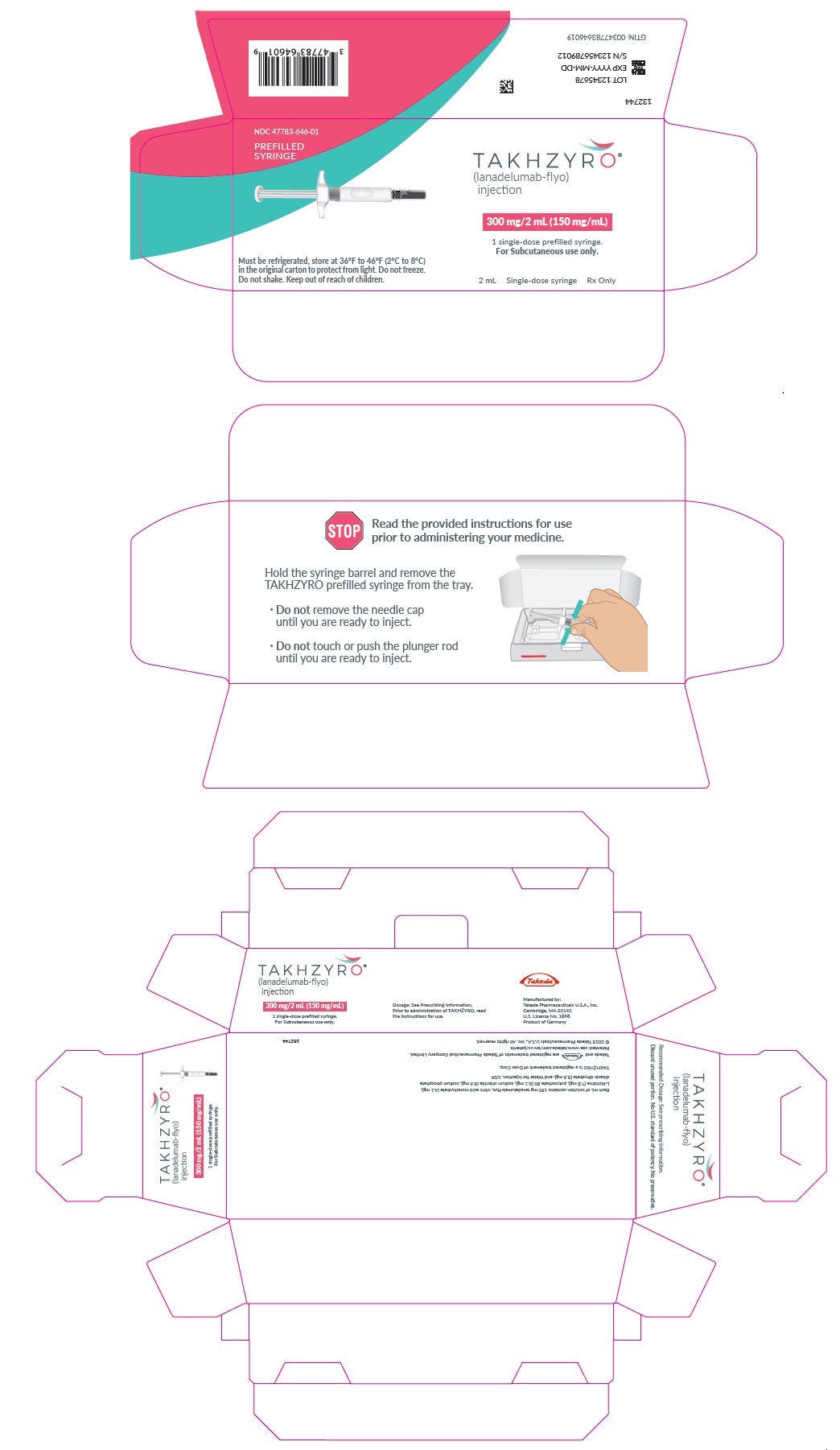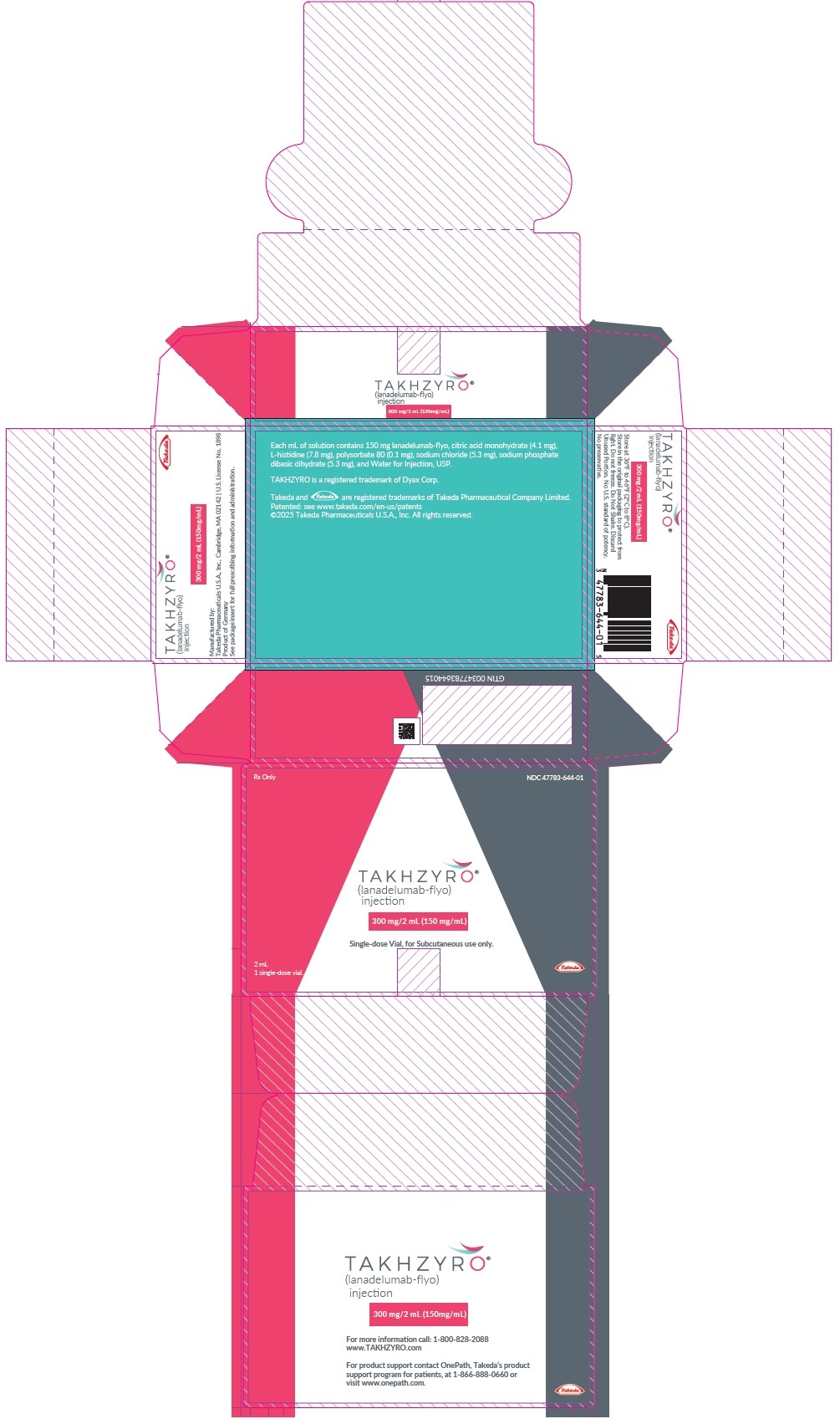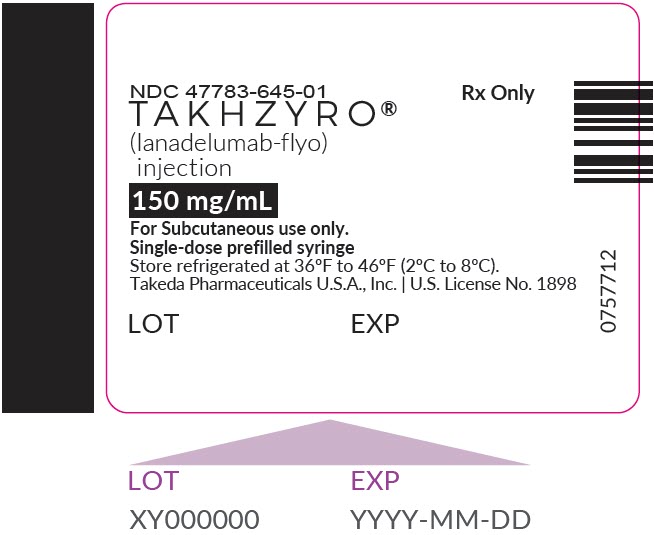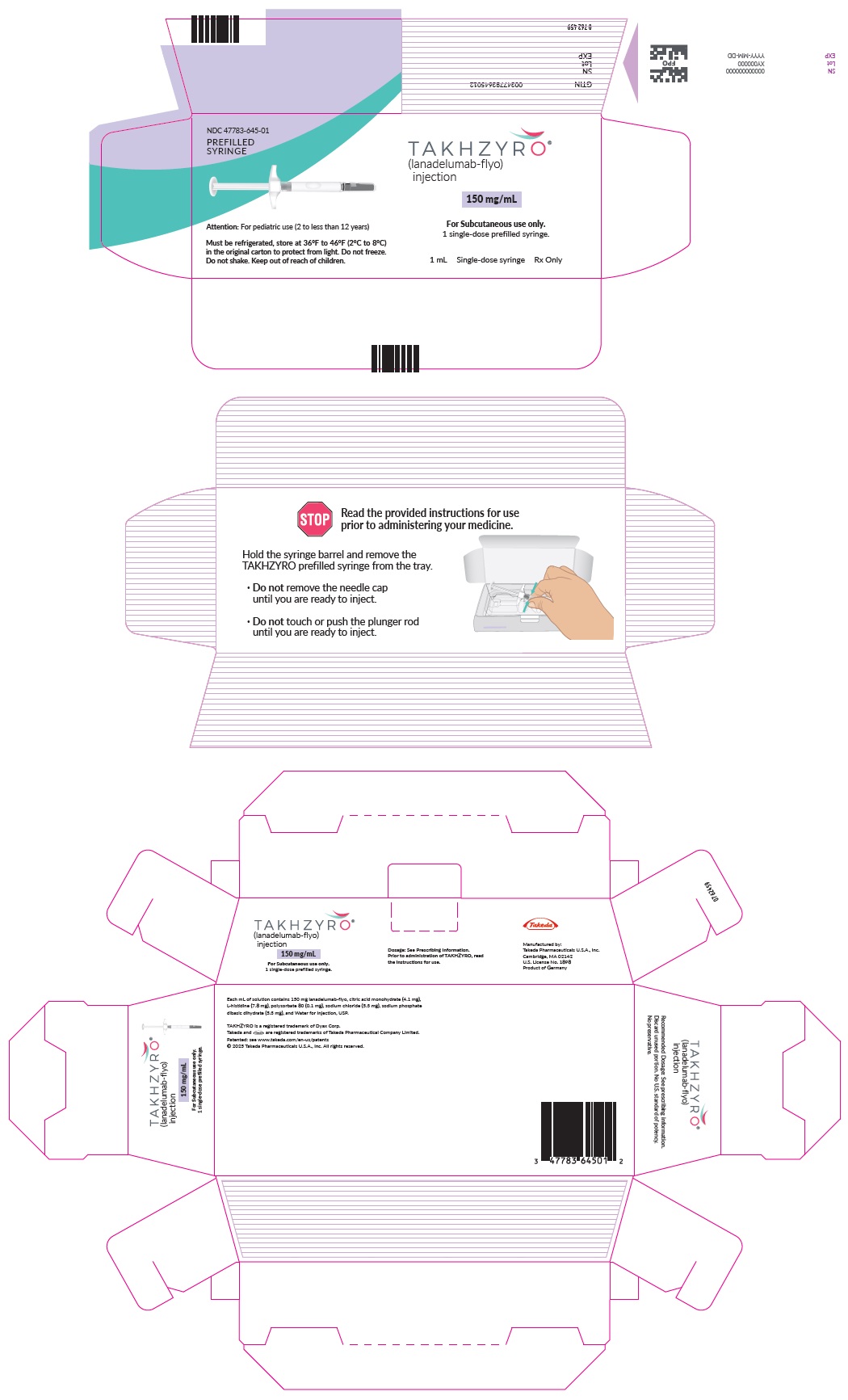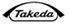 DRUG LABEL: TAKHZYRO
NDC: 47783-646 | Form: SOLUTION
Manufacturer: Takeda Pharmaceuticals America, Inc.
Category: prescription | Type: HUMAN PRESCRIPTION DRUG LABEL
Date: 20250228

ACTIVE INGREDIENTS: lanadelumab 300 mg/2 mL
INACTIVE INGREDIENTS: SODIUM PHOSPHATE, DIBASIC, DIHYDRATE 10.6 mg/2 mL; CITRIC ACID MONOHYDRATE 8.2 mg/2 mL; HISTIDINE 15.6 mg/2 mL; SODIUM CHLORIDE 10.6 mg/2 mL; POLYSORBATE 80 0.2 mg/2 mL

HIGHLIGHTS OF PRESCRIBING INFORMATION

These highlights do not include all the information needed to use TAKHZYRO® safely and effectively. See full prescribing information for TAKHZYRO®.
TAKHZYRO® (lanadelumab-flyo) injection, for subcutaneous use
Initial U.S. Approval: 2018

1 INDICATIONS AND USAGE

TAKHZYRO is a plasma kallikrein inhibitor (monoclonal antibody) indicated for prophylaxis to prevent attacks of hereditary angioedema (HAE) in adult and pediatric patients 2 years and older. (1)

2 DOSAGE AND ADMINISTRATION

For subcutaneous use only.

Recommended Dosage:

- Adult and pediatric patients 12 years of age and older: administer 300 mg every 2 weeks by the patient or caregiver. Dosing interval every 4 weeks may be considered in some patients. (2.1)
- Pediatric patients 6 to less than 12 years of age: administer 150 mg every 2 weeks by a healthcare provider or caregiver. Dosing interval every 4 weeks may be considered in some patients. (2.2)
- Pediatric patients 2 to less than 6 years of age: administer 150 mg every 4 weeks by a healthcare provider or caregiver. (2.2)
- See Full Prescribing Information for Administration Instructions. (2.3)

3 DOSAGE FORMS AND STRENGTHS

Injection:

- 150 mg/1 mL (150 mg/mL) solution in a single-dose prefilled syringe. (3)
- 300 mg/2 mL (150 mg/mL) solution in a single-dose prefilled syringe. (3)
- 300 mg/2 mL (150 mg/mL) solution in a single-dose vial. (3)

4 CONTRAINDICATIONS

None. (4)

5 WARNINGS AND PRECAUTIONS

Hypersensitivity reactions have been observed. In case of a severe hypersensitivity reaction, discontinue TAKHZYRO administration and institute appropriate treatment. (5.1)

6 ADVERSE REACTIONS

The most common adverse reactions (≥10%) are injection site reactions, upper respiratory infections, headache, rash, dizziness, diarrhea, and myalgia. (6.1)

To report SUSPECTED ADVERSE REACTIONS, contact Takeda Pharmaceuticals at 1-877-TAKEDA-7 (1-877-825-3327) or FDA at 1-800-FDA-1088 or www.fda.gov/medwatch.

7 DRUG INTERACTIONS

No dedicated drug interaction studies have been conducted. (7)

FULL PRESCRIBING INFORMATION

1 INDICATIONS AND USAGE

TAKHZYRO® is indicated for prophylaxis to prevent attacks of hereditary angioedema (HAE) in adult and pediatric patients aged 2 years and older.

2 DOSAGE AND ADMINISTRATION

2.1 Recommended Dosage for Adult and Pediatric Patients 12 Years of Age and Older

The recommended starting dosage in adult and pediatric patients 12 years of age and older is 300 mg administered subcutaneously every 2 weeks (q2wks). A dosing interval of 300 mg every 4 weeks (q4wks) is also effective and may be considered if the patient is well-controlled (e.g., attack free) for more than 6 months.

2.2 Recommended Dosage for Pediatric Patients 2 to Less Than 12 Years of Age

Pediatric Patients 6 to Less Than 12 Years of Age

The recommended starting dosage in pediatric patients 6 to less than 12 years of age is 150 mg administered subcutaneously q2wks. A dosing interval of 150 mg q4wks may be considered if the patient is well-controlled (e.g., attack free) for more than 6 months.

Pediatric Patients 2 to Less Than 6 Years of Age

The recommended dosage in pediatric patients 2 to less than 6 years of age is 150 mg administered subcutaneously q4wks.

2.3 Preparation and Administration Instructions

TAKHZYRO is administered subcutaneously only.

TAKHZYRO is intended for administration by a healthcare provider, patient or caregiver.

The patient or caregiver should be trained in subcutaneous injection technique by a healthcare professional.

- Adult and pediatric patients 12 years of age and older: TAKHZYRO may be administered by the patient or caregiver.
- Pediatric patients 2 to less than 12 years of age: TAKHZYRO should be administered by a healthcare provider or caregiver.

Parenteral drug products should be inspected visually for particulate matter and discoloration prior to administration, whenever solution and container permit. Do not use TAKHZYRO if the solution appears discolored or contains visible particles. TAKHZYRO is a clear to slightly opalescent, colorless to slightly yellow solution.

Administration Instructions for Single-Dose Prefilled Syringes

Instruct patients and/or caregiver on proper use of the TAKHZYRO prefilled syringe and assess that they are well trained in subcutaneous injection technique prior to administration by patient and/or caregiver.

Avoid vigorous agitation of the prefilled syringe.

Take the TAKHZYRO prefilled syringe out of the refrigerator 15 minutes before injecting to allow it to equilibrate to room temperature.

Using aseptic technique, inject TAKHZYRO subcutaneously into the abdomen, thigh, or upper arm.

Discard any unused portion of drug remaining in the prefilled syringe.

For detailed instructions on the preparation and administration of TAKHZYRO see Instructions for Use for either single-dose 1 mL prefilled syringe or single-dose 2 mL prefilled syringe.

Administration Instructions for Single-Dose Vial

TAKHZYRO vial is provided as a ready-to-use solution that does not require additional reconstitution or dilution for administration.

Instruct patients and/or caregivers on proper use of TAKHZYRO from a vial and assess that they are well trained in subcutaneous injection technique prior to administration by patient and/or caregiver.

Avoid vigorous agitation of the vial.

Take the TAKHZYRO vial out of the refrigerator 15 minutes before injecting to allow it to equilibrate to room temperature.

Using aseptic technique, withdraw the prescribed dose of TAKHZYRO from the vial using an 18-gauge needle. Change the needle on the syringe to a 27-gauge, ½-inch needle or other needle suitable for subcutaneous injection. Inject TAKHZYRO subcutaneously into the abdomen, thigh, or upper arm. In clinical studies, the majority of patients self-administered TAKHZYRO over 10 to 60 seconds.

TAKHZYRO should be administered within 2 hours of preparing the dosing syringe. After the dosing syringe is prepared, it can be refrigerated at 36°F to 46°F (2°C to 8°C) and must be used within 8 hours.

Discard any unused portions of drug remaining in the vial and dosing syringe.

For detailed instructions on the preparation and administration of TAKHZYRO see single-dose vial Instructions for Use.

3 DOSAGE FORMS AND STRENGTHS

TAKHZYRO is a sterile, preservative-free, clear to slightly opalescent, colorless to slightly yellow solution available in the following presentations.

- Injection: 150 mg/1 mL (150 mg/mL) solution in a single-dose prefilled syringe
- Injection: 300 mg/2 mL (150 mg/mL) solution in a single-dose prefilled syringe
- Injection: 300 mg/2 mL (150 mg/mL) solution in a single-dose vial

4 CONTRAINDICATIONS

None.

5 WARNINGS AND PRECAUTIONS

5.1 Hypersensitivity Reactions

Hypersensitivity reactions have been observed. In case of a severe hypersensitivity reaction, discontinue TAKHZYRO administration and institute appropriate treatment.

6 ADVERSE REACTIONS

6.1 Clinical Trials Experience

Because clinical trials are conducted under widely varying conditions, adverse reaction rates observed in the clinical trials of a drug cannot be directly compared to rates in the clinical trials of another drug and may not reflect the rates observed in practice.

Adult and Pediatric Patients 12 Years of Age and Older

The safety of TAKHZYRO is primarily based on a 26-week, randomized, double-blind, parallel-group and placebo-controlled study (Trial 1) in 125 patients with Type I or II HAE. Eligible patients were also able to participate in an open-label extension study (Trial 2) up to 130 weeks. In Trial 1, a total of 84 patients with HAE aged 12 years and older received at least one dose of TAKHZYRO. Overall, 70% of patients were female and 90% of patients were Caucasian with a mean age of 41 years. The proportion of patients who discontinued study drug prematurely due to adverse events was 1.2% for TAKHZYRO-treated patients and 4.9% for placebo-treated patients. No deaths occurred in the trial.

The safety profile of TAKHZYRO was generally similar across all subgroups of patients, including analysis by age, sex, and geographic region.

Table 1 shows adverse reactions occurring in ≥10% of patients in any TAKHZYRO treatment group that also occurred at a higher rate than in the placebo treatment group in Trial 1.

Table 1 Adverse Reactions Observed in ≥10% of Patients Treated with TAKHZYRO in Trial 1
Adverse Reaction | Placebo (N=41) | TAKHZYRO
Adverse Reaction | Placebo (N=41) | 150 mg q4wks (N=28) | 300 mg q4wks (N=29) | 300 mg q2wks (N=27) | Total (N=84)
Adverse Reaction | n (%) | n (%) | n (%) | n (%) | n (%)
Injection site reactions [Injection site reactions include: pain, erythema, bruising, hematoma, hemorrhage, pruritus, swelling, induration, paresthesia, reaction, warmth, edema and rash.] | 14 (34) | 16 (57) | 13 (45) | 15 (56) | 44 (52)
Upper respiratory infection [Includes upper respiratory infection, viral upper respiratory infection] | 13 (32) | 3 (11) | 9 (31) | 12 (44) | 24 (29)
Headache [Includes headache, tension headache, sinus headache] | 9 (22) | 3 (11) | 6 (21) | 9 (33) | 18 (21)
Rash [Includes rash, rash maculopapular, rash erythematous] | 2(5) | 2 (7) | 3 (10) | 1 (4) | 6 (7)
Dizziness | 0 | 1 (4) | 3 (10) | 1 (4) | 5 (6)
Diarrhea | 2 (5) | 3 (11) | 0 | 1 (4) | 4 (5)
Myalgia | 0 | 1 (4) | 0 | 3 (11) | 4 (5)
N= number of patients; n =number of patients experiencing the event; q2wks = every 2 weeks; q4wks = every 4 weeks

Injection site reactions primarily consisted mainly of pain, erythema, and bruising at the injection site. There was no meaningful difference in injection site reactions with self-administration.

Less Common Adverse Reactions

Other adverse reactions that occurred at a higher incidence in TAKHZYRO-treated patients compared to placebo include hypersensitivity (1% vs 0%), increased aspartate transaminase (2% vs 0%), and increased alanine transaminase (2% vs 0%).

Safety data from the open-label extension study, consisting of 109 rollover patients from Trial 1 and 103 non-rollover HAE patients, is consistent with controlled safety data from Trial 1.

Laboratory Abnormalities

Transaminase elevations

During the placebo-controlled treatment period in Trial 1, the number of TAKHZYRO-treated patients with maximum transaminase (ALT or AST) levels >8, >5, or >3 times the upper limit of normal (ULN) was 1 (1.2%), 0 (0%), or 3 (3.6%) respectively, compared to 0 in the placebo-treated patients. These transaminase elevations were asymptomatic and transient. No patients had elevated total bilirubin >2× ULN. One TAKHZYRO-treated patient permanently discontinued treatment due to elevated transaminases (4.1× ULN AST). None of the patients were reported to have serious adverse reactions of elevated transaminases.

Pediatric Patients 2 to Less Than 12 Years of Age

The safety of TAKHZYRO was evaluated at 150 mg/mL (150 mg q4wks for patients 2 to <6 years or 150 mg q2wks with the option for 150 mg q4wks if the patient is well-controlled for 6 months for patients 6 to <12 years) in an open-label, multicenter study with 21 patients aged 2 to less than 12 years. No new safety signals were observed in these patients.

7 DRUG INTERACTIONS

No dedicated drug interaction studies have been conducted [see Clinical Pharmacology (12.3)].

7.1 Drug-Laboratory Test Interactions

Coagulation tests

TAKHZYRO can increase activated partial thromboplastin time (aPTT) due to an interaction of TAKHZYRO with the aPTT assay. The reagents used in the aPTT laboratory test initiate intrinsic coagulation through the activation of plasma kallikrein in the contact system. Inhibition of plasma kallikrein by TAKHZYRO can increase aPTT in this assay. In Trial 1, prolongation of aPTT (>1× ULN) was observed at one or more time points in 3, 9, and 11 patients treated with TAKHZYRO 150 mg q4wks, 300 mg q4wks, and 300 mg q2wks, respectively, compared to 5 placebo-treated patients. Only one patient in the 300 mg q2wks treatment group experienced transient aPTT prolongation ≥1.5x ULN which was confounded by ongoing heparin therapy. None of the increases in aPTT in patients treated with TAKHZYRO were associated with abnormal bleeding adverse events. There were no differences in INR values between treatment groups.

8 USE IN SPECIFIC POPULATIONS

8.1 Pregnancy

Risk Summary

There are no available data on TAKHZYRO use in pregnant women to inform any drug associated risks. Monoclonal antibodies such as lanadelumab-flyo are transported across the placenta during the third trimester of pregnancy; therefore, potential effects on a fetus are likely to be greater during the third trimester of pregnancy. An enhanced pre-and postnatal development (ePPND) study conducted in pregnant monkeys at doses resulting in exposures of up to 33 times the exposure achieved (on an AUC basis) at the maximum recommended human dose (MRHD) revealed no evidence of harm to the developing fetus.

The background risk of major birth defects and miscarriage for the indicated population is unknown. In the U.S. general population, the estimated background risk of major birth defects and miscarriage in clinically recognized pregnancies is 2 to 4% and 15 to 20%, respectively.

Data

Animal Data

In the ePPND study, pregnant cynomolgus monkeys were administered lanadelumab-flyo once weekly at subcutaneous doses resulting in up to 33 times the exposure at the MRHD (on an AUC basis with maternal subcutaneous doses up to 50 mg/kg/week) from gestation day 20, at the beginning of organogenesis, through to parturition. There were no lanadelumab-flyo-related effects on maintenance of pregnancy or parturition. Maternal lanadelumab-flyo treatment had no effects on embryo-fetal development, survival, growth, or postnatal development of offspring through 3 months of age. Lanadelumab-flyo crossed the placenta in monkeys. Offspring were exposed to lanadelumab-flyo at approximately 50% of the maternal plasma concentration out to postnatal day 21 (PND 21). Lanadelumab-flyo concentrations were approximately equivalent in maternal and offspring plasma at PND 90.

8.2 Lactation

Risk Summary

There are no data on the presence of lanadelumab-flyo in human milk, its effects on the breastfed infant, or its effects on milk production. Lanadelumab-flyo was detected in the milk of lactating cynomolgus monkeys at approximately 0.2% of the maternal plasma concentration. The developmental and health benefits of breastfeeding should be considered along with the mother's clinical need for TAKHZYRO and any potential adverse effects on the breastfed infant from TAKHZYRO or from the underlying maternal condition.

Data

Animal Data

Available pharmacokinetic data in cynomolgus monkeys have shown excretion of lanadelumab-flyo in milk at approximately 0.2% of the maternal plasma level.

8.4 Pediatric Use

The safety and effectiveness of TAKHZYRO for prophylaxis to prevent attacks of hereditary angioedema (HAE) have been established in pediatric patients 2 years of age and older.

Use of TAKHZYRO for this indication in patients 12 years of age and older was supported by a subgroup analysis by age of 10 patients aged 12 to <18 years in Trial 1 (a randomized, double-blind, placebo-controlled parallel-group study in adult and pediatric patients 12 years of age and older with HAE). Results of the subgroup analysis by age were consistent with overall study results. An additional 13 pediatric patients aged 12 to <18 years were enrolled in the open-label extension study [see Adverse Reactions (6.1), Clinical Pharmacology (12.3) and Clinical Studies (14)].

Use of TAKHZYRO for this indication in patients 2 to less than 12 years of age was supported by extrapolation of efficacy data from Trial 1, an adequate and well controlled study in adult and pediatric (12 to less than 18 years of age) patients, with additional pharmacokinetic analyses showing similar drug exposures between adults (>18 years of age) and pediatric patients (2 to less than 12 years of age), and safety and pharmacodynamic data from an open-label, multicenter study in pediatric patients with HAE aged 2 to less than 12 years that enrolled 21 patients (4 patients were aged 2 to less than 6 years and 17 patients were 6 to less than 12 years of age) [see Adverse Reactions (6.1) and Clinical Pharmacology (12.3)]. The pharmacodynamic response observed in this trial for pediatric patients 2 to less than 12 years of age was similar to that seen in adult and pediatric patients 12 years of age and older [see Clinical Pharmacology (12.2)].

The safety and effectiveness of TAKHZYRO in pediatric patients less than 2 years of age have not been established.

8.5 Geriatric Use

The safety and effectiveness of TAKHZYRO were evaluated in a subgroup of patients (N=5) aged ≥65 years in Trial 1. Results of the subgroup analysis by age were consistent with overall study results [see Adverse Reactions (6.1), Clinical Pharmacology (12.3) and Clinical Studies (14)].

10 OVERDOSAGE

There is no clinical experience with overdosage of TAKHZYRO.

11 DESCRIPTION

Lanadelumab-flyo, a plasma kallikrein inhibitor, is a non-plasma derived, recombinant, fully human, monoclonal antibody (IgG1/κ-light chain) produced in Chinese Hamster Ovary (CHO) cells. Based on the amino acid sequence, the molecular weight of the non-glycosylated lanadelumab-flyo is 146 kDa. The calculated molecular mass of the fully reduced light chain is 23 kDa. The calculated molecular mass of the fully reduced and non-glycosylated heavy chain is 49 kDa.

TAKHZYRO (lanadelumab-flyo) injection is a sterile, preservative-free, clear to slightly opalescent, colorless to slightly yellow solution for subcutaneous use.

Each mL of ready-to-use TAKHZYRO solution contains 150 mg of lanadelumab-flyo, citric acid monohydrate (4.1 mg), L-histidine (7.8 mg), polysorbate 80 (0.1 mg), sodium chloride (5.3 mg), sodium phosphate dibasic dihydrate (5.3 mg), and Water for Injection, USP. The solution has a pH of approximately 6.0.

12 CLINICAL PHARMACOLOGY

12.1 Mechanism of Action

Lanadelumab-flyo is a fully human monoclonal antibody (IgG1/κ-light chain) that binds plasma kallikrein and inhibits its proteolytic activity. Plasma kallikrein is a protease that cleaves high-molecular-weight-kininogen (HMWK) to generate cleaved HMWK (cHMWK) and bradykinin, a potent vasodilator that increases vascular permeability resulting in swelling and pain associated with HAE. In patients with HAE due to C1-inhibitor (C1-INH) deficiency or dysfunction, normal regulation of plasma kallikrein activity is not present, which leads to uncontrolled increases in plasma kallikrein activity and results in angioedema attacks. Lanadelumab-flyo decreases plasma kallikrein activity to control excess bradykinin generation in patients with HAE.

12.2 Pharmacodynamics

In adult and pediatric (12 to less than 18 years) patients, concentration-dependent inhibition of plasma kallikrein, measured as reduction of cHMWK levels, was demonstrated after subcutaneous administration of TAKHZYRO 150 mg q4wks, 300 mg q4wks or 300 mg q2wks in patients with HAE.

For pediatric patients 2 to less than 6 years (150 mg q4wks) and 6 to less than 12 years (150 mg q2wks), the observed mean percent change from baseline cHMWK levels was similar to that observed in adult and pediatric (12 to less than 18 years) patients (300 mg q2wks or 300 mg q4wks).

Cardiac Electrophysiology

TAKHZYRO did not prolong the QT/QTc interval.

12.3 Pharmacokinetics

Following subcutaneous administration, the pharmacokinetics of lanadelumab-flyo was approximately dose-proportional in the therapeutic dose range in patients with HAE (Table 2). The pharmacokinetic properties and exposure (steady state) of lanadelumab-flyo in HAE patients, following subcutaneous administration of 150 mg q4wks, 300 mg q4wks and 300 mg q2wks, are provided in Table 2. Following subcutaneous administration of TAKHZYRO, peak plasma concentrations are reached within 5 days, and terminal elimination half-life is ~2 weeks. The anticipated time to reach steady state concentration was approximately 70 days. At steady-state, the mean accumulation ratio is approximately 1.44, 1.42, and 2.43 for dosing regimen of 150 mg q4wks, 300 mg q4wks and 300 mg q2wks, respectively.

Table 2 Mean (SD) Pharmacokinetic Parameters of Lanadelumab-flyo Following Subcutaneous Administration (Trial 1)
Pharmacokinetic Parameters | Lanadelumab-flyo
Pharmacokinetic Parameters | 150 mg q4wks (N=28) | 300 mg q4wks (N=29) | 300 mg q2wks (N=27)
CL/F (L/day) | 0.667 (0.162) | 0.742 (0.239) | 0.809 (0.370)
Vc/F (L) | 14.1 (2.93) | 14.9 (4.45) | 16.6 (4.79)
AUCtau,ss (µg*day/mL) | 233 (56.6) | 441(137) | 408 (138)
Cmax,ss (µg/mL) | 12.0 (3.01) | 23.3 (7.94) | 34.4 (11.2)
Cmin,ss (µg/mL) | 4.81 (1.40) | 8.77 (2.80) | 25.4 (9.18)
tmax (day) | 5.17 (1.09) | 5.17 (1.12) | 4.11 (0.377)
t1/2 (day) | 14.9 (2.00) | 14.2 (1.89) | 15.0 (2.48)
CL/F: apparent clearance; Vc/F: apparent volume of distribution; AUCtau,ss: area under the curve over the dosing interval at steady-state; Cmax,ss: maximum concentration at steady-state; Cmin,ss: minimum concentration at steady state; Tmax: time to maximum concentration; t1/2 terminal elimination half-life.

Specific Populations

Population pharmacokinetic analyses showed that age, gender and race did not meaningfully influence the pharmacokinetics of lanadelumab-flyo after correcting for body weight. Body weight was identified as an important covariate describing the variability of clearance and volume of distribution, resulting in higher exposure (AUC and Cmax) in lighter patients. However, this difference is not considered to be clinically relevant and no dose adjustments are recommended for any of these demographics.

Pediatric Population

Based on population pharmacokinetics (PK) analyses, the geometric mean lanadelumab-flyo average concentration at steady state (Cave) was approximately 25% higher following subcutaneous administration of TAKHZYRO 300 mg q2wks in pediatric patients 12 to less than 18 years of age than the mean Cave in adult patients under the same dosing regimen, due to lower body weight in pediatric patients. Lanadelumab-flyo exposures in pediatric patients 2 to less than 12 years of age receiving TAKHZYRO 150 mg q2wks or q4wks are comparable to those in adult patients receiving TAKHZYRO 300 mg q2wks. The geometric mean lanadelumab-flyo Cave was approximately 7% higher following subcutaneous administration of TAKHZYRO 150 mg q2wks in pediatric patients 6 to less than 12 years of age compared to the mean Cave in adult patients receiving 300 mg q2wks. The mean lanadelumab-flyo Cave was approximately 14% lower following subcutaneous administration of TAKHZYRO 150 mg q4wks in pediatric patients 2 to less than 6 years of age compared to the mean Cave in adult patients receiving 300 mg q2wks.

Renal Impairment

No dedicated studies have been conducted to evaluate the PK of lanadelumab-flyo in renal impairment patients. Based on population pharmacokinetic analysis, renal impairment (estimated GFR: 60 to 89 mL/min/1.73m^2, [mild, N=98] and 30 to 59 mL/min/1.73m^2, [moderate, N=9]) had no effect on the clearance or volume of distribution of lanadelumab-flyo.

Concomitant medications

The use of analgesic, antibacterial, antihistamine, anti-inflammatory and anti-rheumatic medications had no effect on clearance and volume of distribution of lanadelumab-flyo.

For breakthrough HAE attacks, use of rescue medications such as plasma-derived and recombinant C1-INH, icatibant or ecallantide had no effects on clearance and volume of distribution of lanadelumab-flyo.

12.6 Immunogenicity

The observed incidence of anti-drug antibodies is highly dependent on the sensitivity and specificity of the assay. Differences in assay methods preclude meaningful comparisons of the incidence of anti-drug antibodies in the studies described below with the incidence of anti-drug antibodies in other studies, including those of lanadelumab-flyo or of other lanadelumab products.

In Trial 1 with adult and pediatric patients 12 years of age and older, 10 (12%) lanadelumab-flyo-treated and 2 (5%) placebo-treated patients had at least 1 anti-drug antibody (ADA)-positive sample during the 26-week treatment period; antibody titers were low (range: 20 to 1280). The ADA response observed was transient in 2/10 lanadelumab-flyo and 1/2 placebo-treated patients. Pre-existing low titer antibodies were observed in 3 lanadelumab-flyo-treated patients and 1 placebo-treated patient with ADAs. Two patients receiving 150 mg q4wks had low titer antibodies classified as neutralizing.

In an open-label, multicenter study in pediatric patients 2 to less than 12 years of age, 3/20 (15%) lanadelumab-treated patients who completed the study developed ADAs during the 52-week treatment period; all of whom were in the 6 to less than 12 years age group. The ADA response observed was transient in all 3 patients. None of these patients had pre-existing antibodies. One patient had neutralizing antibodies.

The development of ADA including neutralizing antibodies against lanadelumab-flyo did not appear to adversely affect pharmacokinetics (PK), pharmacodynamics (PD), safety or clinical response.

13 NONCLINICAL TOXICOLOGY

13.1 Carcinogenesis, Mutagenesis, Impairment of Fertility

Animal studies have not been conducted to evaluate the carcinogenic potential of lanadelumab-flyo. Published literature supports bradykinin, which is elevated in HAE, as a pro-tumorigenic molecule. However, the malignancy risk in humans from an antibody that inhibits plasma kallikrein activity, such as lanadelumab-flyo, which lowers bradykinin levels, is currently unknown.

Male and female fertility were unaffected based upon no observed adverse histopathological findings in the reproductive organs from sexually mature cynomolgus monkeys that received lanadelumab-flyo for 13 weeks at subcutaneous doses up to 50 mg/kg/week (resulting in approximately 22 times the exposure at the MRHD on an AUC basis).

14 CLINICAL STUDIES

Trial 1 (NCT02586805)

The efficacy of TAKHZYRO for the prevention of angioedema attacks in patients 12 years of age and older with Type I or II HAE was demonstrated in a multicenter, randomized, double-blind, placebo-controlled parallel-group study (Trial 1).

The study included 125 adult and pediatric patients (12 years of age and older) with Type I or II HAE who experienced at least one investigator-confirmed attack per 4 weeks during the run-in period. Patients were randomized into 1 of 4 parallel treatment arms, stratified by baseline attack rate, in a 3:2:2:2 ratio (placebo, lanadelumab-flyo 150 mg q4wks, lanadelumab-flyo 300 mg q4wks, or lanadelumab-flyo 300 mg q2wks by subcutaneous injection) for the 26-week treatment period. Patients ≥18 years of age were required to discontinue other prophylactic HAE medications prior to entering the study; however, all patients were allowed to use rescue medications for treatment of breakthrough HAE attacks.

Overall, 90% of patients had Type I HAE. A history of laryngeal angioedema attacks was reported in 65% of patients and 56% were on prior long-term prophylaxis. During the study run-in period, attack rates of ≥3 attacks/month were observed in 52% of patients overall.

All TAKHZYRO treatment arms produced clinically meaningful and statistically significant reductions in the mean HAE attack rate compared to placebo across all primary and secondary endpoints in the Intent-to-Treat population (ITT) as shown in Table 3.

Table 3 Results of Primary and Secondary Efficacy Measures-ITT Population
Endpoint Statistics | Placebo (N=41) | TAKHZYRO
Endpoint Statistics | Placebo (N=41) | 150 mg q4wks (N=28) | 300 mg q4wks (N=29) | 300 mg q2wks (N=27)
Number of HAE Attacks from Day 0 to 182 [Primary efficacy endpoint.]
LS Mean (95% CI) monthly attack rate [Model-based treatment period HAE attack rate (attacks/4 weeks).] | 1.97 (1.64, 2.36) | 0.48 (0.31, 0.73) | 0.53 (0.36, 0.77) | 0.26 (0.14, 0.46)
% Reduction relative to placebo (95% CI) [Calculated as the ratio of the model-based treatment period HAE attack rates (lanadelumab/placebo) minus 1 multiplied by 100.] |  | 76 (61, 85) | 73 (59, 82) | 87 (76, 93)
Adjusted p-values [Adjusted p-values for multiple testing.] |  | <0.001 | <0.001 | <0.001
Number of HAE Attacks Requiring Acute Treatment from Day 0 to 182
LS Mean (95% CI) monthly attack rate | 1.64 (1.34, 2.00) | 0.31 (0.18, 0.53) | 0.42 (0.28, 0.65) | 0.21 (0.11, 0.40)
% Reduction relative to placebo (95% CI) |  | 81 (66, 89) | 74 (59, 84) | 87 (75, 93)
Adjusted p-values |  | <0.001 | <0.001 | <0.001
Number of Moderate or Severe HAE Attacks from Day 0 to 182
LS Mean (95% CI) monthly attack rate | 1.22 (0.97, 1.52) | 0.36 (0.22, 0.58) | 0.32 (0.20, 0.53) | 0.20 (0.11, 0.39)
% Reduction relative to placebo (95% CI) |  | 70 (50, 83) | 73 (54, 84) | 83 (67, 92)
Adjusted p-values |  | <0.001 | <0.001 | <0.001
CI=confidence interval; LS=least squares.
Note: Results are from a Poisson regression model accounting for over dispersion with fixed effects for treatment group (categorical) and normalized baseline attack rate (continuous), and the logarithm of time in days each patient was observed during the treatment period as an offset variable in the model.

The mean reduction in HAE attack rate was consistently higher across the TAKHZYRO treatment arms compared to placebo regardless of the baseline history of prior long-term prophylaxis, laryngeal attacks, or attack rate during the run-in period.

Additional pre-defined exploratory endpoints included the percentage of patients who were attack free for the entire 26-week treatment period and the percentage of patients achieving threshold (≥50%, ≥70%, ≥90%) reductions in HAE attack rates compared to run-in during the 26-week treatment period. A ≥50% reduction in HAE attack rate was observed in 100% of patients on 300 mg q2wks or q4wks and 89% on 150 mg q4wks compared to 32% of placebo patients. A ≥70% reduction in HAE attack rates was observed in 89%, 76%, and 79% of patients on 300 mg q2wks, 300 mg q4wks, and 150 mg q4wks, respectively, compared to 10% of placebo patients. A ≥90% reduction in HAE attack rates was observed 67%, 55%, and 64% of patients on 300 mg q2wks, 300 mg q4wks, and 150 mg q4wks, respectively, compared to 5% of placebo patients.

The percentage of attack-free patients for the entire 26-week treatment period was 44%, 31%, and 39% in the TAKHZYRO 300 mg q2wks, 300 mg q4wks, and 150 mg q4wks groups respectively, compared to 2% of placebo patients.

Trial 2 (NCT02741596)

Patients who completed Trial 1 were eligible to rollover into an open-label extension study. Rollover patients, regardless of randomization group in Trial 1, received a single dose of TAKHZYRO 300 mg at study entry and were followed until the first HAE attack occurred. All efficacy endpoints were exploratory in this uncontrolled, unblinded study. At week 4 post-dose, approximately 80% of patients who had been in the 300 mg q2wks treatment group (N=25) in Trial 1 remained attack-free. After the first HAE attack, all patients received open-label treatment with TAKHZYRO 300 mg q2wks.

16 HOW SUPPLIED/STORAGE AND HANDLING

How Supplied

TAKHZYRO (lanadelumab-flyo) injection is a ready-to-use, clear to slightly opalescent, colorless to slightly yellow solution supplied in the following presentations.

Single-dose prefilled syringe

- Supplied in a carton containing one single-dose prefilled syringe with a bromobutyl rubber stopper, 27-gauge, ½-inch staked needle and rigid needle cap.
- NDC 47783-645-01: 150 mg/mL prefilled syringe
- NDC 47783-646-01: 300 mg/2 mL (150 mg/mL) prefilled syringe

Single-dose vial

- Supplied in a carton containing one single-dose glass vial with chlorobutyl rubber stopper, aluminum crimp seal and polypropylene flip-off cap.
- NDC 47783-644-01: 300 mg/2 mL (150 mg/mL) vial

Storage and Handling

- Store the prefilled syringes and vials refrigerated at 36°F to 46°F (2°C to 8°C).
- Do not freeze. Do not shake.
- Keep the prefilled syringe and vial in the original carton to protect from light.

17 PATIENT COUNSELING INFORMATION

Advise the patient to read the FDA-approved patient labeling (Patient Information and Instructions for Use).

Hypersensitivity

Advise patients to seek immediate medical attention if they experience any symptoms of serious hypersensitivity reactions [see Warnings and Precautions (5.1)].

Self-Administration:

- Ensure that the patient or caregiver receives clear instructions and training on subcutaneous administration and has demonstrated the ability to perform a subcutaneous injection.
- Instruct patients or caregivers in the technique of proper syringe and needle disposal, and advise them not to reuse these items. Instruct patients or caregivers to dispose needles and syringes in a puncture-resistant container.

For more information, visit www.TAKHZYRO.com

Manufactured by
Takeda Pharmaceuticals U.S.A., Inc.
Cambridge, MA 02142

U.S. License No. 1898

TAKHZYRO is a registered trademark of Dyax Corp.
Takeda and are registered trademarks of Takeda Pharmaceutical Company Limited.

©2025 Takeda Pharmaceuticals U.S.A., Inc. All rights reserved.

PATIENT INFORMATION
TAKHZYRO® (tak-ZYE-roe)
(lanadelumab-flyo)
injection, for subcutaneous use

Read this Patient Information before you start using TAKHZYRO and each time you get a refill. There may be new information. This information does not take the place of talking with your healthcare provider about your medical condition or your treatment.

What is TAKHZYRO?
TAKHZYRO is a prescription medicine used to prevent attacks of Hereditary Angioedema (HAE) in people 2 years of age and older.
It is not known if TAKHZYRO is safe and effective in children under 2 years of age.

Before you use TAKHZYRO, tell your healthcare provider about all of your medical conditions, including if you:

- are pregnant or planning to become pregnant. It is not known if TAKHZYRO can harm your unborn baby.
- are breastfeeding or plan to breastfeed. It is not known if TAKHZYRO passes into your breastmilk. Talk to your healthcare provider about the best way to feed your baby while using TAKHZYRO.

Tell your healthcare provider about all the medicines you take, including prescription medicines, over-the-counter medicines, vitamins, or herbal supplements.

How should I use TAKHZYRO?

- See the detailed Instructions for Use that comes with this patient information leaflet about the right way to prepare and inject TAKHZYRO.
- Use TAKHZYRO exactly as your healthcare provider tells you to use it.
- TAKHZYRO is given as an injection under your skin (subcutaneous) by you or a caregiver.
- Your healthcare provider should show you or your caregiver how to prepare and inject your dose of TAKHZYRO before you inject yourself for the first time.
- Do not try to inject TAKHZYRO unless you have been trained by your healthcare provider.
- Self-injection is not recommended in children (2 to less than 12 years).

What are the possible side effects of TAKHZYRO?
TAKHZYRO may cause serious side effects, including allergic reactions. Allergic reactions may happen with TAKHZYRO. Call your healthcare provider or get emergency help right away if you have any of the following symptoms:

- wheezing
- difficulty breathing
- chest tightness
- fast heartbeat

- faintness
- rash
- hives

The most common side effects of TAKHZYRO are:

- injection site reactions (pain, redness, and bruising)
- upper respiratory infections
- headache
- rash
- dizziness
- diarrhea
- muscle aches

Tell your healthcare provider if you have any side effect that bothers you or that does not go away. These are not all the possible side effects of TAKHZYRO. For more information, ask your healthcare provider or pharmacist.
Call your doctor for medical advice about side effects. You may report side effects to FDA at 1-800-FDA-1088.

General information about the safe and effective use of TAKHZYRO.
Medicines are sometimes prescribed for purposes other than those listed in a Patient Information leaflet. Do not use TAKHZYRO for a condition for which it is not prescribed. Do not give TAKHZYRO to other people, even if they have the same symptoms that you have. It may harm them. You can ask your pharmacist or healthcare provider for information about TAKHZYRO that is written for health professionals.

What are the ingredients in TAKHZYRO?
Active ingredient: lanadelumab
Inactive ingredients: citric acid monohydrate, L-histidine, sodium chloride, sodium phosphate dibasic dihydrate and water for injection.
Manufactured by:
Takeda Pharmaceuticals U.S.A., Inc.
Cambridge, MA 02142
U.S. License No. 1898
TAKHZYRO is a registered trademark of Dyax Corp. Takeda and are registered trademarks of Takeda Pharmaceutical Company Limited.
©2025 Takeda Pharmaceuticals U.S.A., Inc. All rights reserved.
For more information, visit www.TAKHZYRO.com or call 1-877-TAKEDA-7 (1-877-825-3327).

This Patient Information has been approved by the U.S. Food and Drug Administration.

Revised: 1/2025

INSTRUCTIONS FOR USE

TAKHZYRO® (tak-ZYE-roe)
(lanadelumab-flyo)
injection, for subcutaneous use
single-dose 1 mL preﬁlled syringe

This Instructions for Use contains information on how to inject TAKHZYRO. Please make sure to read, understand, and follow the Instructions for Use before injecting TAKHZYRO.

A healthcare provider should show you how to prepare and inject TAKHZYRO properly before you use it for the first time. Contact your healthcare provider if you have any questions.

Important information:

- TAKHZYRO is a ready to use prefilled syringe (Figure A) for injection under the skin (subcutaneous) to be given to children by their healthcare provider or caregiver. Self-injection is not recommended in children (2 to less than 12 years of age).
- Each TAKHZYRO prefilled syringe contains one 150 mg/1 mL dose. The TAKHZYRO prefilled syringe is for single use only.

Figure A: TAKHZYRO prefilled syringe

Storing TAKHZYRO:

- Store the TAKHZYRO prefilled syringe in the refrigerator at 36°F to 46°F (2°C to 8°C).
  Do not freeze.
- Store the TAKHZYRO prefilled syringe in the original carton to protect it from light.
- Throw away (discard) the TAKHZYRO prefilled syringe if it has been kept out of the refrigerator, frozen, or not kept in the original carton protected from light.
- Do not shake the TAKHZYRO prefilled syringe.
  Keep the TAKHZYRO prefilled syringe and all medicines out of the reach of children.

Step 1: Prepare for your injection

a. Gather an alcohol swab, cotton ball or gauze pad, adhesive bandage, and sharps disposal container (Figure B) and place the supplies on a clean, flat, surface in a well-lit area. These supplies are not included in the TAKHZYRO carton.

Figure B: Supplies

b. Remove the TAKHZYRO prefilled syringe carton from the refrigerator 15 minutes before injecting.
  - Do not use if the seal on the carton is open or broken.
  - Your medicine is sensitive to warm temperatures. Do not use heat sources such as a microwave or hot water to warm your TAKHZYRO prefilled syringe.

c. Open the carton. Hold the syringe barrel and remove the TAKHZYRO prefilled syringe from the tray (Figure C).
  - Do not remove the needle cap until you are ready to inject.
  - Do not touch or push the plunger rod until you are ready to inject.

Figure C: Remove prefilled syringe

d. Wash your hands with soap and water (Figure D). Dry your hands completely.
  - Do not touch any surface or body part after washing your hands before the injection.

Figure D: Wash hands

e. Check the expiration date (EXP) on the syringe barrel (Figure E).
  - Do not use the TAKHZYRO prefilled syringe if the expiration date has passed. If the TAKHZYRO prefilled syringe is expired throw it away (discard) in a sharps container and contact your healthcare provider.

Figure E: Location of expiration date

f. Inspect the TAKHZYRO prefilled syringe for any damage. The medicine inside the syringe barrel should be colorless to slightly yellow (Figure F).
  - Do not use the TAKHZYRO prefilled syringe if the syringe is damaged or cracked.
  - Do not use the TAKHZYRO prefilled syringe if the medicine is discolored, cloudy, or has flakes or particles in it.
  - You may see air bubbles in the TAKHZYRO prefilled syringe. This is normal and will not affect your dose.
  If you cannot use the prefilled syringe, contact your healthcare provider.

Figure F: Inspect the prefilled syringe

Step 2: Select and prepare injection site

a. TAKHZYRO should be injected by a healthcare provider or caregiver into the following sites only (Figure G):
  - stomach area (abdomen)
  - thighs
  - upper arms
  - Do not inject into an area where the skin is irritated, red, bruised, or infected.
  - The area you choose for injection should be at least 2 inches away from any scars or belly button (navel).

Important:
Rotate injection sites to keep skin healthy. Each new injection should be given at least 1 inch from the last site you used.

Figure G: Injection sites

b. Clean the injection site with an alcohol swab and allow it to dry completely (Figure H).
  - Do not fan or blow on the clean site.
  - Do not touch the clean site again before giving your injection.

Figure H: Clean injection site

c. Firmly hold the middle of the TAKHZYRO prefilled syringe with one hand, and with the other hand, gently pull the needle cap straight off (Figure I).
  - Do not touch or push the plunger rod until you are ready to inject.
  - Do not use the TAKHZYRO prefilled syringe if it has been dropped without the needle cap on.
  - Do not use the TAKHZYRO prefilled syringe if the needle looks damaged or bent.
  - Do not touch the needle or allow the needle to touch anything.
  You may see air bubbles, this is normal. Do not try to remove the air bubbles.

Figure I: Remove needle cap

d. Throw away the needle cap in your trash or in your sharps container.
  - Do not recap the needle to avoid a needle-stick injury.

Step 3: Inject TAKHZYRO

a. Grip the TAKHZYRO prefilled syringe in one hand like a pencil (Figure J). Avoid touching the needle or pushing on the plunger rod.

Figure J: Grip prefilled syringe

b. With your other hand, gently pinch a 1-inch fold of skin at the cleaned injection site.
  - Keep pinching until the injection is complete and the needle is removed (Figure K).

Figure K: Pinch a 1-inch fold of skin

c. Using a quick dart-like motion, insert the needle at a 45-to-90-degree angle. Make sure to keep the needle in place (Figure L).
  Important: Inject directly into the fatty layer under the skin (subcutaneous injection).

Figure L: Insert the needle

d. Slowly push the plunger rod all the way down until it stops (Figure M).
  Important: Do not remove the needle until all of the medicine is injected and the syringe barrel is empty.
  When the injection is complete, you will see the stopper at the bottom of the syringe barrel (Figure N).
  Figure N: Stopper at the bottom of the syringe barrel

Figure M: Push the plunger rod all the way down

e. Slowly remove the needle while maintaining the syringe at the same angle. Gently release the fold of skin.

f. Press a cotton ball or gauze pad over the injection site if needed and hold for 10 seconds.
  - Do not rub the injection site. There may be a small amount of blood where you injected. This is normal.
  - Cover the injection site with an adhesive bandage if needed.

Step 4: Throw away (dispose of) TAKHZYRO prefilled syringe

a. Put your used TAKHZYRO prefilled syringe in a sharps disposal container right away after use (Figure O).
  - Do not recap the needle to avoid a needle-stick injury.
  - Do not reuse the TAKHZYRO prefilled syringe or any of your injection supplies.
  - Do not throw away (dispose of) the TAKHZYRO prefilled syringe in your household trash.
  - Do not touch the needle.

FDA-cleared sharps containers are generally available through pharmacies, medical supply companies, healthcare providers, and online.

Figure O: Dispose in a sharps container

  - If you do not have an FDA-cleared sharps container, you may use a household container that is:
    - made of a heavy-duty plastic
    - can be closed with a tight-fitting, puncture-resistant lid, without sharps being able to come out,
    - upright and stable during use
    - leak-resistant, and
    - properly labeled to warn of hazardous waste inside the container.
  - When your sharps disposal container is almost full, you will need to follow your community guidelines for the right way to dispose of your sharps disposal container. There may be state or local laws about how you should throw away used needles and syringes. For more information about safe sharps disposal, and for specific information about sharps disposal in the state that you live in, go to FDA's website at:
    http://www.fda.gov/safesharpsdisposal.
  - Important: Always keep the sharps disposal container out of the reach of children.
  - Do not dispose of your used sharps disposal container in your household trash unless your community guidelines permit this. Do not recycle your used sharps disposal container.

Questions?

For product or service-related questions, call 1-877-TAKEDA-7 (1-877-825-3327) or go to www.TAKHZYRO.com.

Manufactured by:
Takeda Pharmaceuticals U.S.A., Inc.
Cambridge, MA 02142
U.S. License No. 1898

TAKHZYRO is a registered trademark of Dyax Corp. Takeda and are registered trademarks of Takeda Pharmaceutical Company Limited.
©2025 Takeda Pharmaceuticals U.S.A., Inc. All rights reserved.

This Instructions for Use has been approved by the U.S. Food and Drug Administration.

Approved: 1/2025

INSTRUCTIONS FOR USE

TAKHZYRO® (tak-ZYE-roe)
(lanadelumab-flyo)
injection, for subcutaneous use
single-dose preﬁlled syringe

This Instructions for Use contains information on how to inject TAKHZYRO. Please make sure to read, understand, and follow the Instructions for Use before injecting TAKHZYRO.

A healthcare provider should show you how to prepare and inject TAKHZYRO properly before you use it for the first time. Contact your healthcare provider if you have any questions.

Important information:

- TAKHZYRO is a ready to use prefilled syringe (Figure A) for injection under the skin (subcutaneous) to be given by your healthcare provider, caregiver, or by yourself.
- Each TAKHZYRO prefilled syringe contains one 300 mg/2 mL dose. The TAKHZYRO prefilled syringe is for single use only.

Figure A: TAKHZYRO prefilled syringe

Storing TAKHZYRO:

- Store the TAKHZYRO prefilled syringe in the refrigerator at 36°F to 46°F (2°C to 8°C).
  Do not freeze.
- Store the TAKHZYRO prefilled syringe in the original carton to protect it from light.
- Throw away (discard) the TAKHZYRO prefilled syringe if it has been kept out of the refrigerator, frozen, or not kept in the original carton protected from light.
- Do not shake the TAKHZYRO prefilled syringe.
  Keep the TAKHZYRO prefilled syringe and all medicines out of the reach of children.

Step 1: Prepare for your injection

a. Gather an alcohol swab, cotton ball or gauze pad, adhesive bandage, and sharps disposal container (Figure B) and place the supplies on a clean, flat, surface in a well-lit area. These supplies are not included in the TAKHZYRO carton.

Figure B: Supplies

b. Remove the TAKHZYRO prefilled syringe carton from the refrigerator 15 minutes before injecting.
  - Do not use if the seal on the carton is open or broken.
  - Your medicine is sensitive to warm temperatures. Do not use heat sources such as a microwave or hot water to warm your TAKHZYRO prefilled syringe.

c. Open the carton. Hold the syringe barrel and remove the TAKHZYRO prefilled syringe from the tray (Figure C).
  - Do not remove the needle cap until you are ready to inject.
  - Do not touch or push the plunger rod until you are ready to inject.

Figure C: Remove prefilled syringe

d. Wash your hands with soap and water (Figure D). Dry your hands completely.
  - Do not touch any surface or body part after washing your hands before the injection.

Figure D: Wash hands

e. Check the expiration date (EXP) on the syringe barrel (Figure E).
  - Do not use the TAKHZYRO prefilled syringe if the expiration date has passed. If the TAKHZYRO prefilled syringe is expired throw it away (discard) in a sharps container and contact your healthcare provider.

Figure E: Location of expiration date

f. Inspect the TAKHZYRO prefilled syringe for any damage. The medicine inside the syringe barrel should be colorless to slightly yellow (Figure F).
  - Do not use the TAKHZYRO prefilled syringe if the syringe is damaged or cracked.
  - Do not use the TAKHZYRO prefilled syringe if the medicine is discolored, cloudy, or has flakes or particles in it.
  - You may see air bubbles in the TAKHZYRO prefilled syringe. This is normal and will not affect your dose.
  If you cannot use the prefilled syringe, contact your healthcare provider.

Figure F: Inspect the prefilled syringe

Step 2: Select and prepare injection site

a. TAKHZYRO should be injected into the following sites only (Figure G):
  - stomach area (abdomen)
  - thighs
  - upper arms (only if a healthcare provider or caregiver is giving you the injection)
  - Do not inject into an area of your body where the skin is irritated, red, bruised, or infected.
  - The area you choose for injection should be at least 2 inches away from any scars or your belly button (navel).
  Important:
  Rotate injection sites to keep skin healthy. Each new injection should be given at least 1 inch from the last site you used.

Figure G: Injection sites

b. Clean the injection site with an alcohol swab and allow it to dry completely (Figure H).
  - Do not fan or blow on the clean site.
  - Do not touch the clean site again before giving your injection.

Figure H: Clean injection site

c. Firmly hold the middle of the TAKHZYRO prefilled syringe with one hand, and with the other hand, gently pull the needle cap straight off (Figure I).
  - Do not touch or push the plunger rod until you are ready to inject.
  - Do not use the TAKHZYRO prefilled syringe if it has been dropped without the needle cap on.
  - Do not use the TAKHZYRO prefilled syringe if the needle looks damaged or bent.
  - Do not touch the needle or allow the needle to touch anything.
  You may see air bubbles, this is normal. Do not try to remove the air bubbles.

Figure I: Remove needle cap

d. Throw away the needle cap in your trash or in your sharps container.
  - Do not recap the needle to avoid a needle-stick injury.

Step 3: Inject TAKHZYRO

a. Grip the TAKHZYRO prefilled syringe in one hand like a pencil (Figure J). Avoid touching the needle or pushing on the plunger rod.

Figure J: Grip prefilled syringe

b. With your other hand, gently pinch a 1-inch fold of skin at the cleaned injection site.
  - Keep pinching until the injection is complete and the needle is removed (Figure K).

Figure K: Pinch a 1-inch fold of skin

c. Using a quick dart-like motion, insert the needle at a 45-to-90-degree angle. Make sure to keep the needle in place (Figure L).
  Important: Inject directly into the fatty layer under the skin (subcutaneous injection).

Figure L: Insert the needle

d. Slowly push the plunger rod all the way down until it stops (Figure M).
  Important: Do not withdraw the needle until all of the medicine is injected and the syringe barrel is empty.
  When the injection is complete, you will see the stopper at the bottom of the syringe barrel (Figure N).
  Figure N: Stopper at the bottom of the syringe barrel

Figure M: Push the plunger rod all the way down

e. Slowly withdraw the needle while maintaining the syringe at the same angle. Gently release the fold of skin.

f. Press a cotton ball or gauze pad over the injection site if needed and hold for 10 seconds.
  - Do not rub the injection site. There may be a small amount of blood where you injected. This is normal.
  - Cover the injection site with an adhesive bandage if needed.

Step 4: Throw away (dispose of) TAKHZYRO prefilled syringe

a. Put your used TAKHZYRO prefilled syringe in a sharps disposal container right away after use (Figure O).
  - Do not recap the needle to avoid a needle-stick injury.
  - Do not reuse the TAKHZYRO prefilled syringe or any of your injection supplies.
  - Do not throw away (dispose of) the TAKHZYRO prefilled syringe in your household trash.
  - Do not touch the needle.

FDA-cleared sharps containers are generally available through pharmacies, medical supply companies, healthcare providers, and online.

Figure O: Dispose in a sharps container

  - If you do not have an FDA-cleared sharps container, you may use a household container that is:
    - made of a heavy-duty plastic
    - can be closed with a tight-fitting, puncture-resistant lid, without sharps being able to come out,
    - upright and stable during use
    - leak-resistant, and
    - properly labeled to warn of hazardous waste inside the container.
  - When your sharps disposal container is almost full, you will need to follow your community guidelines for the right way to dispose of your sharps disposal container. There may be state or local laws about how you should throw away used needles and syringes. For more information about safe sharps disposal, and for specific information about sharps disposal in the state that you live in, go to FDA's website at:
    http://www.fda.gov/safesharpsdisposal.
  - Important: Always keep the sharps disposal container out of the reach of children.
  - Do not dispose of your used sharps disposal container in your household trash unless your community guidelines permit this. Do not recycle your used sharps disposal container.

Questions?

For product or service-related questions, call 1-877-TAKEDA-7 (1-877-825-3327) or go to www.TAKHZYRO.com.

Manufactured by:
Takeda Pharmaceuticals U.S.A., Inc.
Cambridge, MA 02142
U.S. License No. 1898

TAKHZYRO is a registered trademark of Dyax Corp. Takeda and are registered trademarks of Takeda Pharmaceutical Company Limited.
©2025 Takeda Pharmaceuticals U.S.A., Inc. All rights reserved.

This Instructions for Use has been approved by the U.S Food and Drug Administration.

Approved: 1/2025

INSTRUCTIONS FOR USE TAKHZYRO® (tak-ZYE-roe) (lanadelumab-flyo) injection, for subcutaneous use

Be sure that you read, understand, and follow the Instructions for Use before injecting TAKHZYRO. A healthcare provider should show you how to prepare and inject TAKHZYRO properly before you use it for the first time. Contact your healthcare provider if you have any questions.

Important information:

- TAKHZYRO is a ready-to-use solution for injection under the skin (subcutaneous). It is supplied in a single-dose, glass vial.
- Your healthcare provider will prescribe the dose that you should take.
- Only use the syringes, transfer needles, and injection needles that your healthcare provider prescribes.
- Only use the syringes, transfer needles and injection needles 1 time. Throw away (dispose of) any used syringes and needles.

Storing TAKHZYRO:

- Store TAKHZYRO in the refrigerator at 36°F to 46°F (2°C to 8°C). Do not freeze.
- Store TAKHZYRO in the original carton to protect the vial from light.
- Do not shake TAKHZYRO.
- Keep TAKHZYRO and all medicines out of the reach of children.

Supplies needed for your TAKHZYRO Injection

1 Vial containing TAKHZYRO

TAKHZYRO Instructions for Use

2 Alcohol wipes

1 Empty 3 mL syringe

18G Transfer needle (longer needle)
Do not use the transfer needle to inject TAKHZYRO.

27G ½-inch Injection needle (shorter needle).
Do not use the injection needle to withdraw TAKHYZRO from the vial.

Sharps disposal container. See "STEP 6" at the end of this Instructions for Use.

STEP 1: Prepare for your injection

- Gather all supplies and place them on a well-lighted flat work surface.
- Take the vial out of the refrigerator 15 minutes before use and allow it to reach room temperature before preparing an injection.
- Check the expiration date on the box and vial label of TAKHZYRO. Do not use if the expiration date has passed.
- Check the supplies for damage. Do not use if they appear damaged.
- Clean your work area and wash your hands before preparing your dose. Do not touch any surface or body part, especially your face, after washing your hands before injection.
- Remove the vial from the packaging. Do not use the vial if the plastic cap covering is missing.

- Gently turn the vial upside down (invert) 3 to 5 times to mix the medicine. Do not shake to avoid foaming.
- Look at the medicine in the vial for visible particles or a change in the color. Medicine should be colorless to slightly yellow. Do not use if you see particles or a change in color.

Important: Do not shake.

- Remove the plastic cap from the medicine vial. Do not remove the medicine vial rubber stopper.

- Place the vial on a flat surface. Clean the medicine vial rubber stopper with an alcohol wipe and allow it to dry.

STEP 2: Attach transfer needle to syringe

- Screw the 18G transfer needle to the 3mL syringe.

Important: Do not remove the transfer needle cap from the needle when attaching to the syringe.

- Pull back the plunger to fill the syringe with air equal to the amount of medicine in the vial.

- Hold the syringe by the barrel with one hand and the transfer needle cap with the other hand.
- Pull off the transfer needle cap straight away from the syringe and away from your body. Do not pull on the plunger. Place the transfer needle cap down on a clean flat surface.
- Do not touch the needle tip.

STEP 3: Transfer TAKHZYRO into syringe and switch to the injection needle

- Keep the vial on the flat surface and insert the transfer needle into the center of the rubber stopper.
- Push the plunger down to inject air into the vial and hold the plunger down.

- Slowly turn the vial upside down with transfer needle and syringe attached. Pull back on the plunger to withdraw the full dose in the vial.

Important: Be sure to keep the tip of the transfer needle in the medicine to avoid drawing air in as you pull back the plunger.

- Remove large air bubbles by gently tapping on the syringe barrel with your fingers until the bubbles rise to the top of the syringe.
- Slowly push the plunger, allowing air to go back into the vial, until the medicine reaches the top of the syringe.
- Repeat these steps until large air bubbles are removed.

Important: Check again to make sure you have the right amount of medicine in your syringe. If you do not have enough medicine, pull back on the plunger again while keeping the needle in the medicine to get your full dose.

- Return the vial to an upright position.
- Without removing the needle from the vial, unscrew the syringe by holding the needle hub and turning the syringe counter clockwise.
- Return the syringe to an upright position.

- Throw away the 18G transfer needle and the vial in a sharps disposal container (See Step 6).

- Screw the 27G ½-inch injection needle to the syringe.

Important: Do not remove the needle cap from the injection needle when attaching to the syringe.
Do not use the transfer needle to inject TAKHZYRO as this may cause harm such as pain and bleeding.

STEP 4: Select and prepare injection site

- TAKHZYRO can be self-injected in your stomach (abdomen) or thigh. If given by a caregiver, TAKHZYRO may also be injected in the upper arm.
- Clean your injection site with an alcohol wipe and allow it to dry completely.

Important:

- You should use a different injection site each time you receive an injection to keep your skin healthy.
- The area you choose for injection should be at least 2 inches (5 cm) away from any scars or your belly button (navel). Do not choose an area that is bruised, swollen, or painful.
- TAKHZYRO should be given within 2 hours of preparing the dosing syringe at room temperature. After the dosing syringe is prepared, it can be refrigerated at 36°F to 46°F (2°C to 8°C) and must be used within 8 hours of preparation. Take the dosing syringe out of the refrigerator 15 minutes before use and allow it to reach room temperature prior to injecting.

STEP 5: Inject TAKHZYRO

- Hold the syringe by the barrel with one hand and the injection needle cap with the other hand.
- Pull off the injection needle cap straight away from the syringe and away from your body. Do not pull on the plunger. Do not touch the needle tip or allow it to touch any other surface.

- Gently pinch about 1 inch of skin at your cleaned chosen injection site and insert the needle.

Important: Be sure to inject under the skin which is not too shallow (skin layer) or too deep (muscle).

- Push the plunger slowly until no medicine remains in the syringe. Release the skin fold and gently remove the needle. Do not recap the needle.

STEP 6: THROW AWAY (DISPOSE OF) NEEDLE AND SYRINGE

- Place the 27G ½-inch Injection needle and the syringe in a sharps container.
- If you do not have a FDA-cleared sharps disposal, you may use a household container that is:
  - Made of heavy-duty plastic,
  - Can be closed with a tight fitting, puncture-resistant lid, without sharps being able to come out,
  - Upright and stable during use,
  - Leak-resistant, and
- Properly labeled to warn of hazardous waste inside the container.
- When your sharps disposal container is almost full, you will need to follow your community guidelines for the right way to dispose of your sharps disposal container. There may be state or local laws about how you should throw away used needles and syringes. For more information about safe sharps disposal, and for specific information about sharps in the state you live in, go to the FDA's website at:
  http://www.fda.gov/safesharpsdisposal.
  Important: Always keep the sharps disposal container out of the reach of children.

For more information, visit www.TAKHZYRO.com

This Instructions for Use has been approved by the U.S. Food and Drug Administration.

Manufactured by:

Takeda Pharmaceuticals U.S.A., Inc.
Cambridge, MA 02142

U.S. License No: 1898

TAKHZYRO is a registered trademark of Dyax Corp. Takeda and are registered trademarks of Takeda Pharmaceutical Company Limited.

©2025 Takeda Pharmaceuticals U.S.A., Inc. All rights reserved.

Approved: 1/2025

PRINCIPAL DISPLAY PANEL - 2 mL Syringe Carton

NDC 47783-646-01

PREFILLED
SYRINGE

TAKHZYRO®
(lanadelumab-flyo)
injection

300 mg/2 mL (150 mg/mL)

1 single-dose prefilled syringe.
For Subcutaneous use only.

Must be refrigerated, store at 36°F to 46°F (2°C to 8°C)
in the original carton to protect from light. Do not freeze.
Do not shake. Keep out of reach of children.

2 mL
Single-dose syringe
Rx Only

PRINCIPAL DISPLAY PANEL - 2 mL Vial Carton

Rx Only
NDC 47783-644-01

TAKHZYRO®
(lanadelumab-flyo)
injection

300 mg/2 mL (150 mg/mL)

Single-dose Vial, for Subcutaneous use only.

2 mL
1 single-dose vial.

Takeda

PRINCIPAL DISPLAY PANEL - 150 mg/mL Syringe Label

NDC 47783-645-01

TAKHZYRO®
(lanadelumab-flyo)
injection

150 mg/mL

For Subcutaneous use only.
Single-dose prefilled syringe
Store refrigerated at 36°F to 46°F (2°C to 8°C).
Takeda Pharmaceuticals U.S.A., Inc. | U.S. License No. 1898

LOT
EXP

Rx Only

0757712

PRINCIPAL DISPLAY PANEL - 150 mg/mL Syringe Carton

NDC 47783-645-01

PREFILLED
SYRINGE

TAKHZYRO®
(lanadelumab-flyo)
injection

150 mg/mL

Attention: For pediatric use (2 to less than 12 years)

For Subcutaneous use only.
1 single-dose prefilled syringe.

Must be refrigerated, store at 36°F to 46°F (2°C to 8°C)
in the original carton to protect from light. Do not freeze.
Do not shake. Keep out of reach of children.

1 mL
Single-dose syringe
Rx Only